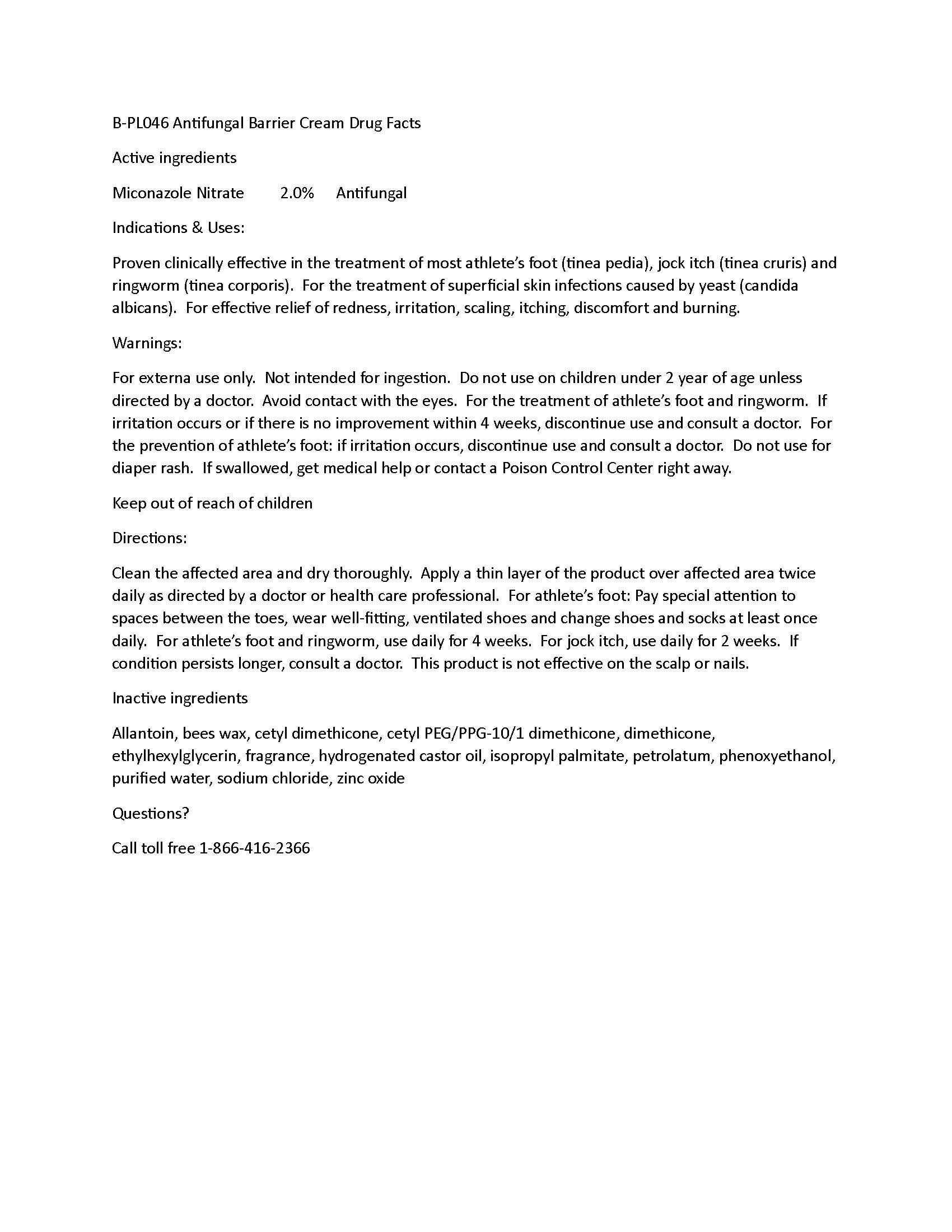 DRUG LABEL: Private Label Antifungal Barrier Cream
NDC: 60232-0046 | Form: CREAM
Manufacturer: Swiss-American CDMO, LLC
Category: otc | Type: HUMAN OTC DRUG LABEL
Date: 20250509

ACTIVE INGREDIENTS: MICONAZOLE NITRATE 200 g/1000 g
INACTIVE INGREDIENTS: WATER; ALLANTOIN; PHENOXYETHANOL; ETHYLHEXYLGLYCERIN; PETROLATUM; DIMETHICONE 1000; BEESWAX; HYDROGENATED CASTOR OIL; ZINC OXIDE; ISOPROPYL PALMITATE; CETYL DIMETHICONE 25; CETYL PEG/PPG-10/1 DIMETHICONE (HLB 5)

Private Label Antifungal Barrier Cream

Warnings

For external use only. Not intended for ingestion. Do not use on children under 2 year of age unless directed by a doctor. Avoid contact with the eyes. For the treatment of athlete’s foot and ringworm. If irritation occurs or if there is no improvement within 4 weeks, discontinue use and consult a doctor. For the prevention of athlete’s foot: if irritation occurs, discontinue use and consult a doctor. Do not use for diaper rash. If swallowed, get medical help or contact a Poison Control Center right away.

Active Ingredients

Miconazole Nitrate 2.0%

Indications & Uses

Proven clinically effective in the treatment of most athlete’s foot (tinea pedia), jock itch (tinea cruris) and ringworm (tinea corporis). For the treatment of superficial skin infections caused by yeast (candida albicans). For effective relief of redness, irritation, scaling, itching, discomfort and burning.

Directions

Clean the affected area and dry thoroughly. Apply a thin layer of the product over affected area twice daily as directed by a doctor or health care professional. For athlete’s foot: Pay special attention to spaces between the toes, wear well-fitting, ventilated shoes and change shoes and socks at least once daily. For athlete’s foot and ringworm, use daily for 4 weeks. For jock itch, use daily for 2 weeks. If condition persists longer, consult a doctor. This product is not effective on the scalp or nails.

Keep out of reach of children

Inactive ingredients

Allantoin, bees wax, cetyl dimethicone, cetyl PEG/PPG-10/1 dimethicone, dimethicone, ethylhexylglycerin, fragrance, hydrogenated castor oil, isopropyl palmitate, petrolatum, phenoxyethanol, purified water, sodium chloride, zinc oxide

Questions?

Call toll free 1-866-416-2366

Purpose

Antifungal